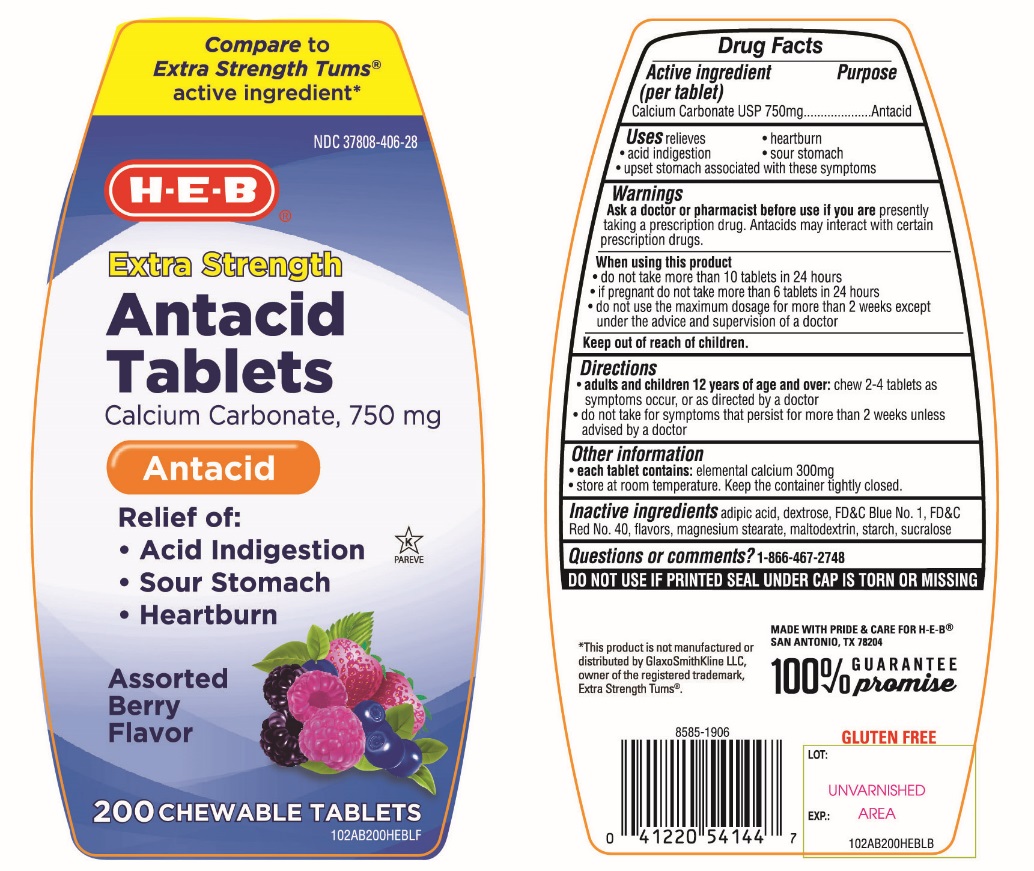 DRUG LABEL: HEB Antacid Extra Strength

NDC: 37808-406 | Form: TABLET, CHEWABLE
Manufacturer: HEB
Category: otc | Type: HUMAN OTC DRUG LABEL
Date: 20251003

ACTIVE INGREDIENTS: CALCIUM CARBONATE 750 mg/1 1
INACTIVE INGREDIENTS: ADIPIC ACID; DEXTROSE, UNSPECIFIED FORM; FD&C BLUE NO. 1; FD&C RED NO. 40; MAGNESIUM STEARATE; MALTODEXTRIN; STARCH, CORN; SUCRALOSE

H-E-B Extra Strength Antacid Calcium Carbonate Drug Facts

Active ingredient (per tablet)

Calcium Carbonate USP 750mg

Purpose

Antacid

Uses

relieves

- heartburn
- acid indigestion
- sour stomach
- upset stomach associated with these symptoms

Ask a doctor or pharmacist before use if you are

presently taking a prescription drug. Antacids may interact with certain prescription drugs.

When using this product

- do not take more than 10 tablets in 24 hours
- if pregnant do not take more than 6 tablets in 24 hours
- do not use the maximum dosage for more than 2 weeks except under the advice and supervision of a doctor

Directions

- adults and children 12 years of age and over:chew 2-4 tablets as symptoms occur, or as directed by a doctor.
- do not take for symptoms that persist for more than 2 weeks unless advised by a doctor

Other information

- each tablet contains:elemental calcium 300mg
- store at room temperature. Keep the container tightly closed.

Inactive Ingredients

adipic acid, dextrose, FD&C Blue No. 1, FD&C Red No. 40, flavor, magnesium stearate, maltodextrin, starch, sucralose.

Questions or comments?

1-866-467-2748

Safety Sealed

DO NOT USE IF PRINTED SEAL UNDER CAP IS TORN OR MISSING

Package/Label Principal Display Panel

H-E-B®

NDC# 37808-406-28

Compare To Extra Strength Tums®active ingredient*

Extra Strength

Antacid Tablets

Calcium Carbonate, 750 mg/Antacid

RELIEF OF:

- Acid Indigestion
- Sour Stomach
- Heartburn

Assorted Berry Flavors

GLUTEN FREE

200 CHEWABLE TABLETS

K PAREVE

100% GUARANTEE promise

MADE WITH PRIDE & CARE FOR H-E-B®SAN ANTONIA, TX 78204

*This product is not manufactured or distributed by GlaxoSmithKline LLC, owner of the registered trademark, Extra Strength Tums®.